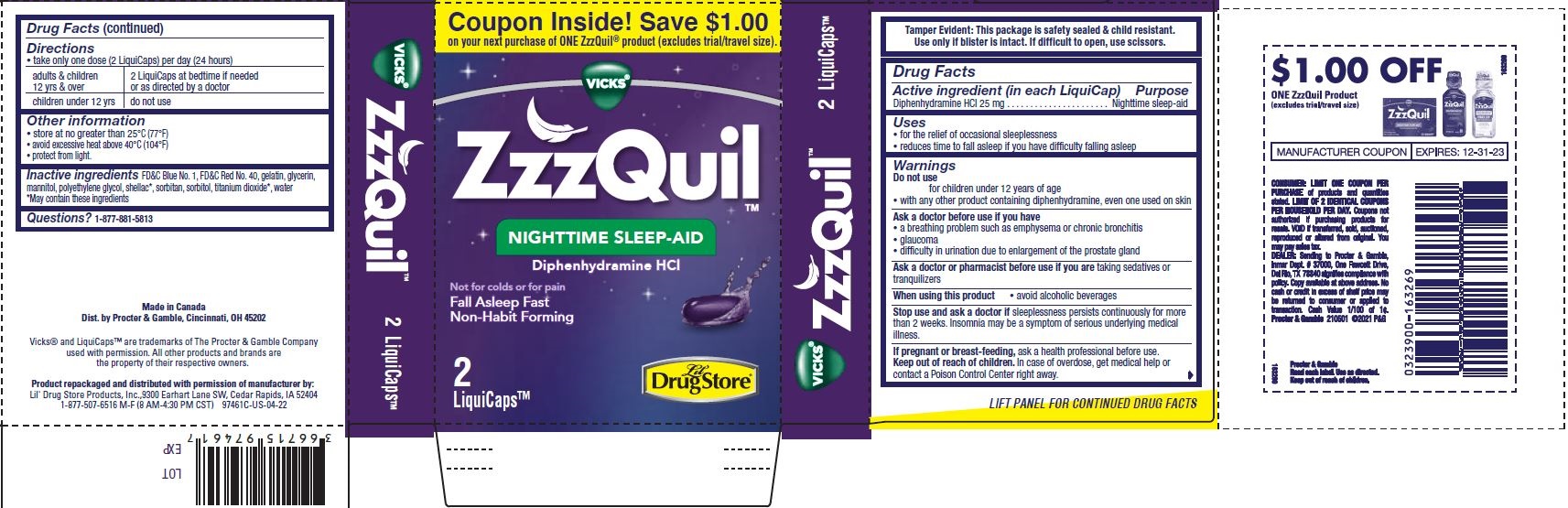 DRUG LABEL: ZzzQuil
NDC: 66715-9746 | Form: CAPSULE, LIQUID FILLED
Manufacturer: Lil' Drug Store Products, Inc.
Category: otc | Type: HUMAN OTC DRUG LABEL
Date: 20241118

ACTIVE INGREDIENTS: DIPHENHYDRAMINE HYDROCHLORIDE 50 mg/2 1
INACTIVE INGREDIENTS: FD&C BLUE NO. 1; GELATIN, UNSPECIFIED; GLYCERIN; PROPYLENE GLYCOL; WATER; FD&C RED NO. 40; SORBITOL; TITANIUM DIOXIDE

ZzzQuil™

Drug Facts

Active ingredient (in each LiquiCap)

Diphenhydramine hydrochloride 25 mg

Purpose

Nighttime sleep-aid

Uses

- for the relief of occasional sleeplessness
- reduces time to fall asleep if you have difficulty falling asleep

Warnings

Do not use

- for children under 12 years of age
- with any other product containing diphenhydramine, even one used on skin

Ask a doctor before use if you have

- a breathing problem such as emphysema or chronic bronchitis
- glaucoma
- difficulty in urination due to enlargement of the prostate gland

Ask a doctor or pharmacist before use if you are taking sedatives or tranquilizers

When using this product

- avoid alcoholic beverages

Stop use and ask a doctor if sleeplessness persists continuously for more than 2 weeks. Insomnia may be a symptom of serious underlying medical illness.

PREGNANCY OR BREAST FEEDING

If pregnant or breast-feeding, ask a health professional before use.

Keep out of reach of children. In case of overdose, get medical help or contact a Poison Control Center right away.

Directions

- take only one dose (2 LiquiCaps) per day (24 hours)

adults & children 12 yrs & over | 2 LiquiCaps at bedtime if needed or as directed by a doctor
children under 12 yrs | do not use

Other information

- store at no greater than 25°C (77°F)
- avoid excessive heat above 40°C (104°F)
- protect from light.

Inactive ingredients

FD&C Blue No. 1, FD&C Red No. 40, gelatin, glycerin, mannitol, polyethylene glycol, shellac*, sorbitan, sorbitol titanium dioxide*, water

*May contain these ingredients

Questions or comments?

1-877-881-5813

Made in Canada

Dist. by Procter & Gamble, Cincinnati, OH 45202

Vicks® and LiquiCaps™ are trademarks of The Procter & Gamble Company
used with permission. All other products and brands are
the property of their respective owners.

Product repackaged and distributed with permission of manufacturer by:
Lil' Drug Store Products, Inc., 9300 Earhart Lane SW, Cedar Rapids, IA 52404

1-877-507-6516 M-F (8 AM-4:30 PM CST) 97461C-US-04-22

PRINCIPAL DISPLAY PANEL - 2 LiquiCap Blister Pack Carton

Coupon Inside! Save $1.00

on your next purchase of ONE ZzzQuil® product (excludes trial/travel size).

VICKS®

ZzzQuil™
NIGHTTIME SLEEP-AID
Diphenhydramine HCl

Not for colds or pain

Fall Asleep Fast

Non-Habit Forming

[LiquiCap image]

2

LiquiCaps™

[Lil' Drug Store® logo]